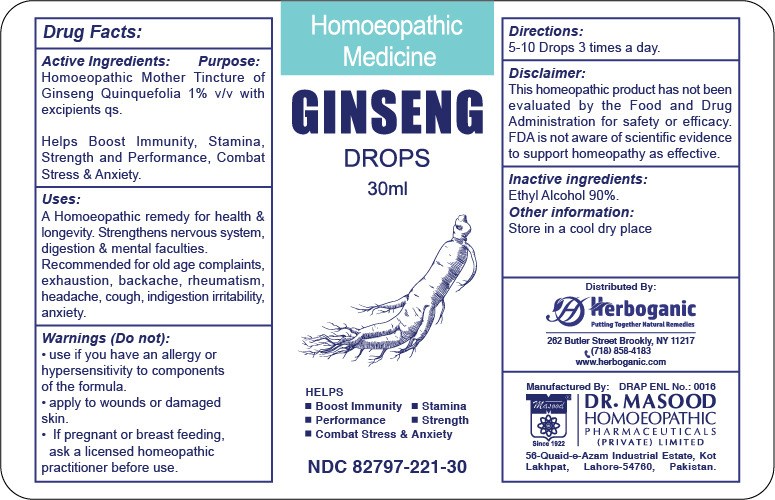 DRUG LABEL: Ginseng Drops
NDC: 82797-221 | Form: SOLUTION
Manufacturer: Dr. Masood Homeopathic Pharmaceuticals Private Limited
Category: homeopathic | Type: HUMAN OTC DRUG LABEL
Date: 20240509

ACTIVE INGREDIENTS: PANAX QUINQUEFOLIUS WHOLE 1 [hp_X]/30 mL
INACTIVE INGREDIENTS: ALCOHOL 29.7 mL/30 mL

Dosage and Adminstration

5-10 drops three times a day.

Inactive Ingredient:

Ethyl Alcohil 90%

Active Ingredients:

Panax quinquefolium (American Ginseng) 1% v/v

Keep out of the reach of children:

Keep this and all medicnes out of the reach of children

Indications and Usage :

A homeopathic remedy for health and longevity. strengthens nervous sytem, digestion an dmental faculties,

Recommended for old age complaints, exhaustion, backache, rheumatism, headache, cough, indigestion, irritability and anxiety

Purpose:

Helps boost Immunity, Stamina, Strength and Performance

Combats Stress and Anxiety

Warnings:

Do not:

- use if you have an allergy or hypersensitivity to components of the formula
- apply to wound or damaged skin
- use if pregnant or nursing

Stop use and ask a doctor if:

- condition worsens
- If symptoms persists for more than 7 days